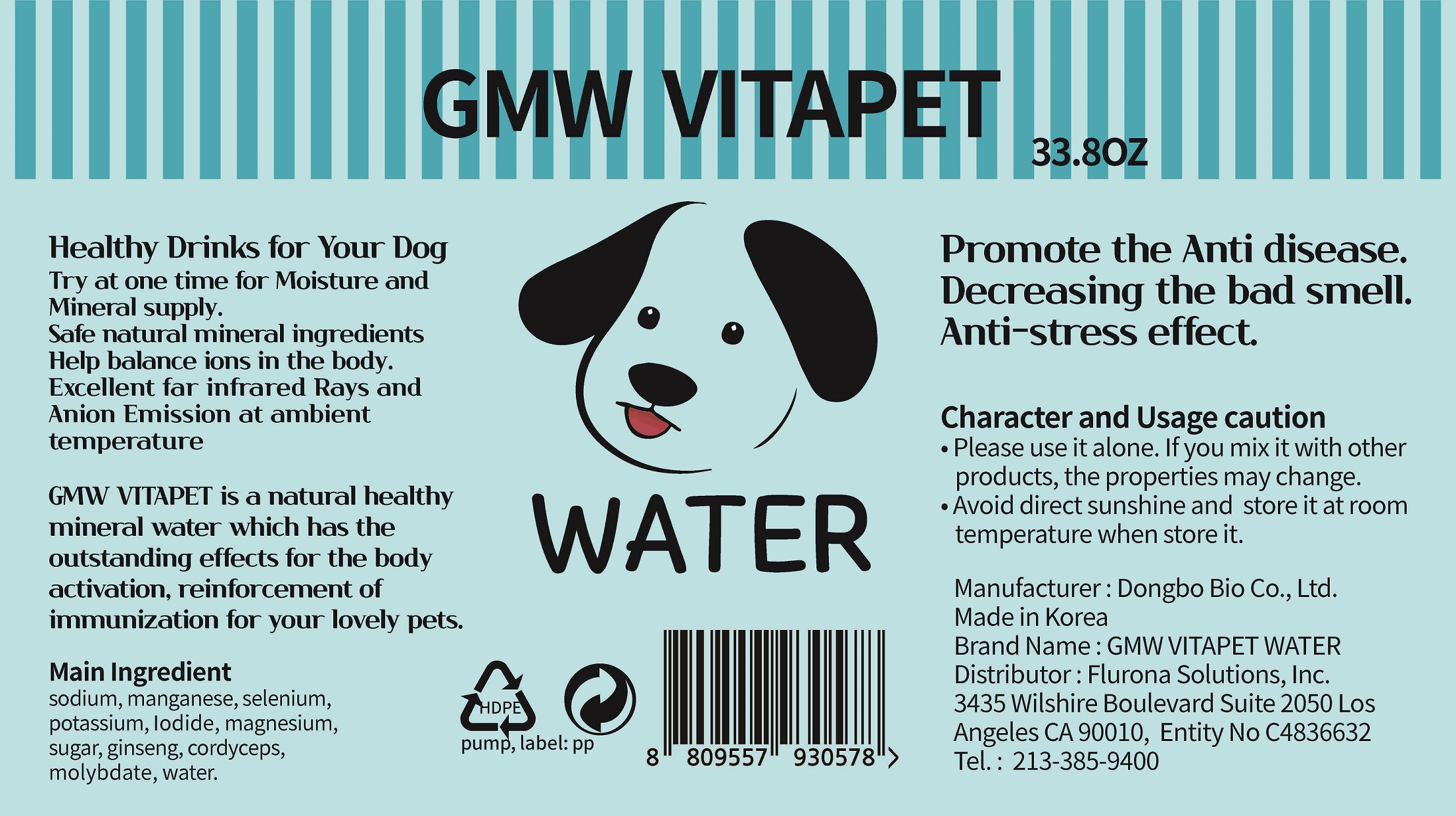 DRUG LABEL: GMW VITAPET WATER
NDC: 74651-0009 | Form: LIQUID
Manufacturer: DONGBO BIO CO.,LTD
Category: animal | Type: OTC ANIMAL DRUG LABEL
Date: 20220504

ACTIVE INGREDIENTS: SODIUM 0.49967 g/1000 mL
INACTIVE INGREDIENTS: WATER; MANGANESE; SELENIUM; POTASSIUM; IODIDE ION; MAGNESIUM; ASIAN GINSENG

ACTIVE INGREDIENT

sodium

INACTIVE INGREDIENT

manganese, selenium, potassium, Iodide, magnesium, sugar, ginseng, cirdyceps, molybdate, water

PURPOSE

promote the anti disease, decreasing the bad smell, anti-stress effect

WARNINGS

■ if following abnormal symptoms persist, discontinue use

Irritation around the eyes, ears, mucous membranes, including the mouth, under the skin irritation and rashes

■ Stop immediately and consult a doctor if you experience

1) Hypersensitivity symptoms such as erythema, itching and dermatitis.

2) Skin Irritation

3) Following Instructions when using medication

Avoid getting into the eyes (if contact occurs, wash well with clean water)

■ Be careful not to inhale or use excessively for a long time (ingesting ethanol repeatedly causes irritation to mucous membranes and headaches or other symptoms may appear. When used repeatedly in the same area, skin irritation may occur.

Keep Out of Reach of Children

INDICATIONS AND USAGE

Please use it alone. If you mix it with other products, the properties may change.

Avoid direct sunshine and store it at room temperature when store it.

DOSAGE AND ADMINISTRATION

for oral use only